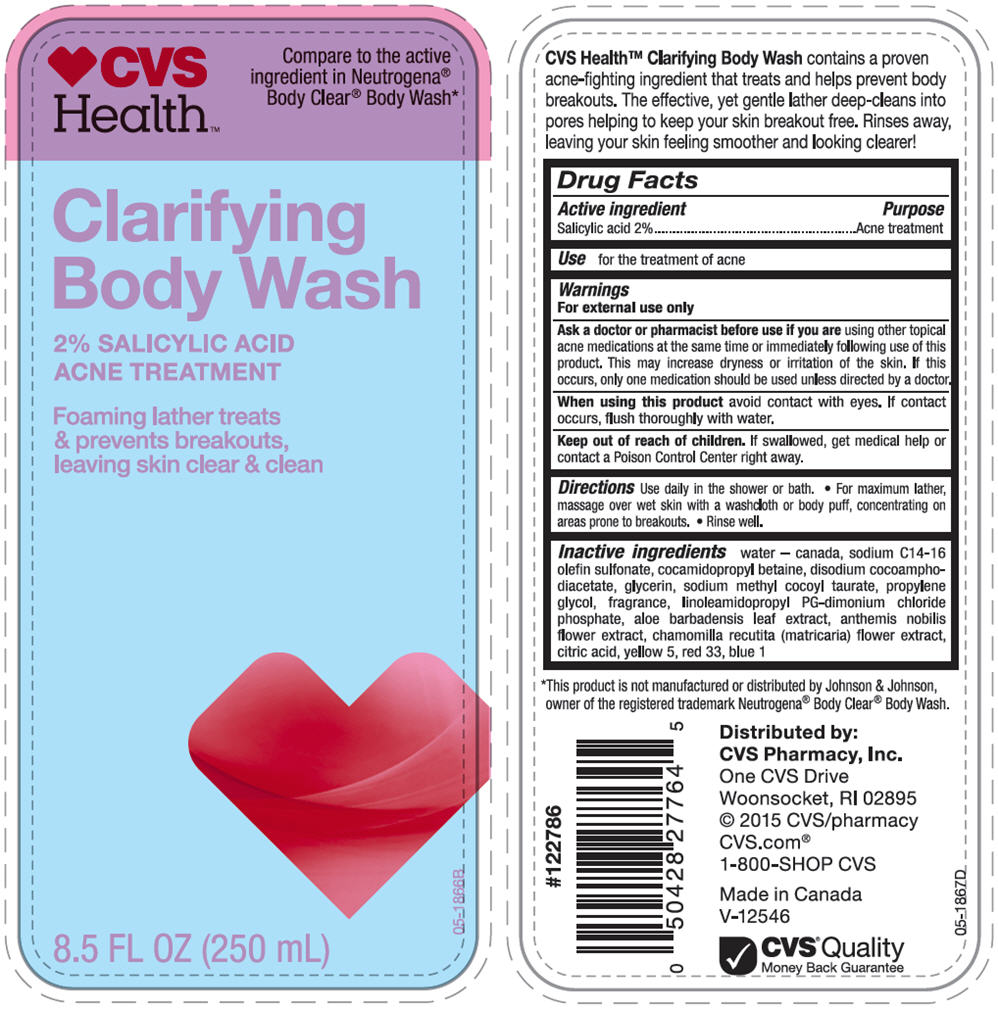 DRUG LABEL: CVS Clarifying Body Wash
NDC: 69842-583 | Form: LOTION
Manufacturer: CVS Health
Category: otc | Type: HUMAN OTC DRUG LABEL
Date: 20241112

ACTIVE INGREDIENTS: Salicylic Acid 20 mg/1 mL
INACTIVE INGREDIENTS: Water; Sodium C14-16 Olefin Sulfonate; Cocamidopropyl Betaine; Disodium Cocoamphodiacetate; Glycerin; Sodium Methyl Cocoyl Taurate; Propylene Glycol; Linoleamidopropyl Propylene Glycol-Dimonium Chloride Phosphate; Aloe Vera Leaf; Chamaemelum Nobile Flower; Chamomile; Citric Acid Monohydrate; Fd&C Yellow No. 5; D&C Red No. 33; Fd&C Blue No. 1

CVS Clarifying Body Wash
Acne Treatment

Drug Facts

Active ingredients

Salicylic Acid 2.0%

Purpose

Acne Treatment

Use

For the treatment of acne

Warnings

For external use only

Ask a doctor or pharmacist before use if you are using other topical acne medications at the same time or immediately following use of this product. This may increase dryness or irritation of the skin. If this occurs, only one medication should be used unless directed by a doctor.

When using this product avoid contact with eyes. If contact occurs, flush thoroughly with water.

Keep out of reach of children. If swallowed, get medical help or contact a Poison Control Center right away.

Directions

- Use daily in the shower or bath
- For maximum lather, massage over wet skin with a washcloth or body puff, concentrating on areas prone to breakouts
- Rinse well.

Inactive ingredients

Water, Sodium C14-16 Olefin Sulfonate, Cocamidopropyl Betaine, Disodium Cocoamphodiacetate, Glycerin, Sodium Methyl Cocoyl Taurate, Propylene Glycol, Fragrance, Linoleamidopropyl PG-Dimonium Chloride Phosphate, Aloe Barbadensis Leaf Extract, Anthemis Nobilis Flower Extract, Chamomilla Recutita (Matricaria) Flower Extract, Citric Acid, Yellow 5, Red 33, Blue 1

Distributed by:
CVS Pharmacy, Inc.
One CVS Drive
Woonsocket, RI 02895

PRINCIPAL DISPLAY PANEL - 250 mL Bottle Label

♥ CVS
Health™

Compare to the active
ingredient in Neutrogena®
Body Clear® Body Wash*

Clarifying
Body Wash

2% SALICYLIC ACID
ACNE TREATMENT

Foaming lather treats
& prevents breakouts,
leaving skin clear & clean

8.5 FL OZ (250 mL)

05-1866B